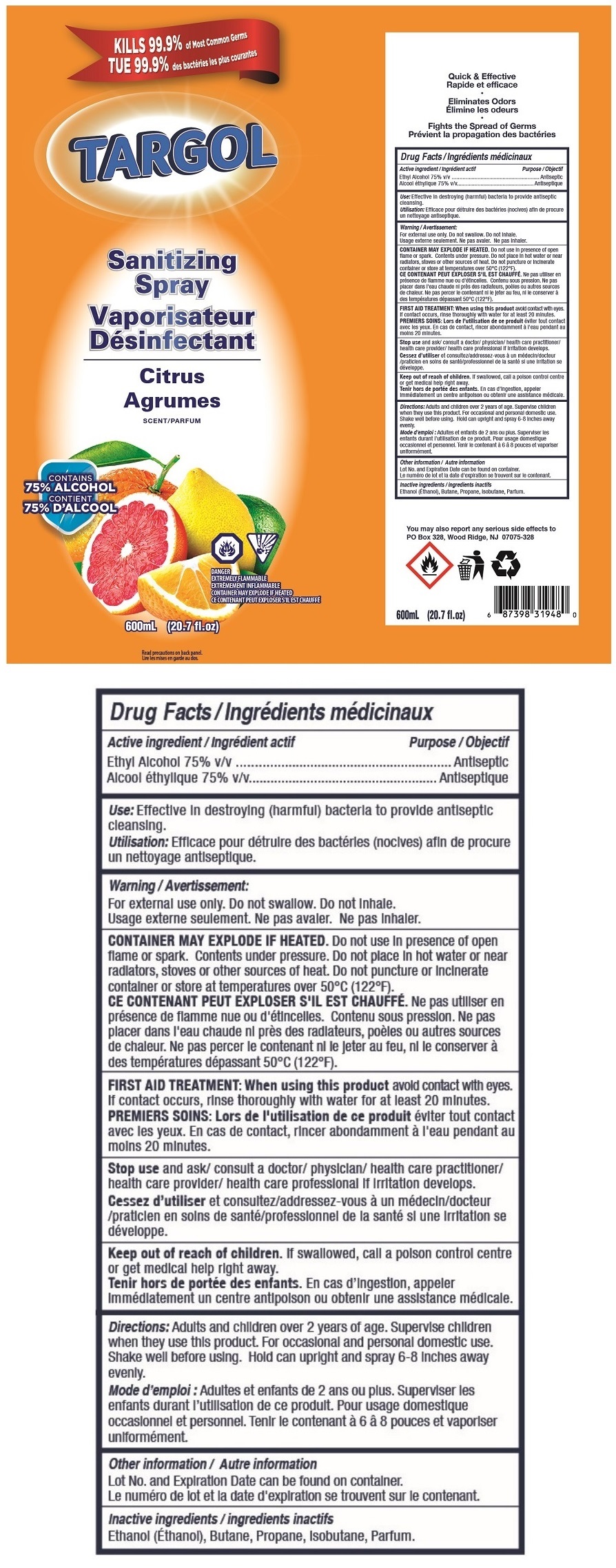 DRUG LABEL: TARGOL Sanitizing Citrus
NDC: 80793-012 | Form: AEROSOL, SPRAY
Manufacturer: HEDEF KIMYA SANAYI VE TICARET ANONIM SIRKETI
Category: otc | Type: HUMAN OTC DRUG LABEL
Date: 20201202

ACTIVE INGREDIENTS: ALCOHOL 75 mL/100 mL
INACTIVE INGREDIENTS: BUTANE; PROPANE; ISOBUTANE

TARGOL Sanitizing Spray Citrus

Active ingredient

Ethyl Alcohol 75% v/v

Purpose

Antiseptic

Use:

Effective in destroying (harmful) bacteria to provide antiseptic cleansing.

Warning

For external use only. Do not swallow. Do not inhale.

CONTAINER MAY EXPLODE IF HEATED. Do not use in presence of open flame or spark. Contents under pressure. Do not place in hot water or near radiators, stoves or other sources of heat. Do not puncture or incinerate container or store at temperatures over 50°C (122°F).

FIRST AID TREATMENT: When using this product avoid contact with eyes. If contact occurs, rinse thoroughly with water for at least 20 minutes.

Stop use and ask/ consult a doctor/ physician/ health care practitioner/ health care provider/ health care professional if irritation develops.

Keep out of reach of children. If swallowed, call a poison control centre or get medical help right away.

Directions:

Adults and children over 2 years of age. Supervise children when they use this product. For occasional and personal domestic use. Shake well before using. Hold can upright and spray 6-8 inches away evenly.

Other information

Lot No. and Expiration Date can be found on container.

Inactive ingredients

Ethanol (Éthanol), Butane, Propane, Isobutane, Parfum.

KILLS 99.9% of Most Common Germs

Citrus

SCENT/PARFUM

CONTAINS 75% ALCOHOL

DANGER

EXTREMELY FLAMMABLE

CONTAINER MAY EXPLODE IF HEATED

Read precautions on back panel.

Quick & Effective

Eliminates Odors

Fights the Spread of Germs

You may also report any serious side effects to PO Box 328, Wood Ridge, NJ 07075-328